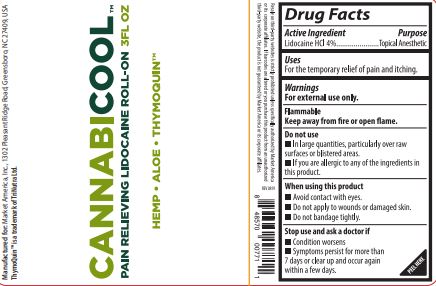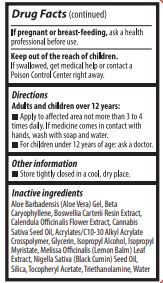 DRUG LABEL: Cannabicool Pain Relieving Lidocaine Roll-On
NDC: 76209-567 | Form: GEL
Manufacturer: Market America, Inc.
Category: otc | Type: HUMAN OTC DRUG LABEL
Date: 20220114

ACTIVE INGREDIENTS: LIDOCAINE HYDROCHLORIDE 40 mg/1 g
INACTIVE INGREDIENTS: ALOE VERA LEAF; CARYOPHYLLENE; FRANKINCENSE; CALENDULA OFFICINALIS FLOWER; CANNABIS SATIVA SEED OIL; CARBOMER INTERPOLYMER TYPE B (ALLYL PENTAERYTHRITOL CROSSLINKED); GLYCERIN; ISOPROPYL ALCOHOL; ISOPROPYL MYRISTATE; MELISSA OFFICINALIS LEAF; NIGELLA SATIVA SEED OIL; SILICON DIOXIDE; .ALPHA.-TOCOPHEROL ACETATE; TROLAMINE; WATER

Cannabicool Pain Relieving Lidocaine Roll-On

Active Ingredient

Lidocaine HCl 4%

Purpose

Topical Anesthetic

Uses

For the temporary relief of pain and itching.

WARNINGS

For external use only.

SAFE HANDLING WARNING

Flammable

Keep away from fire or open flame.

Do not use

- In large quantities, particularly over raw surfaces or blistered areas.
- If you are allergic to any of the ingredients in this product.

When using this product

- Avoid contact with eyes.
- Do not apply to wounds or damaged skin.
- Do not bandage tightly.

Stop use and ask a doctor if

- Condition worsens.
- Symptoms persist for more than 7 days or clear up and occur again within a few days.

PREGNANCY OR BREAST FEEDING

If pregnant or breast-feeding, ask a health professional before use.

Keep out of reach of children

If swallowed, get medical help or contact a Poison Control Center right away.

Directions

Adults and children over 12 years:

- Apply to affected area not more than 3 to 4 times daily. If medicine comes in contact with hands, wash with soap and water.
- For children under 12 years of age: ask a doctor.

Other information

- Store tightly closed in a cool, dry place.

Inactive ingredients

Aloe Barbadensis (Aloe Vera) Gel, Beta Caryophyllene, Boswellia Carterii Resin Extract, Calendula Officinalis Flower Extract, Cannabis Sativa Seed Oil, Acrylates/c10-30 Alkyl Acrylate Crosspolymer, Glycerin, Isopropyl Alcohol, Isopropyl Myristate, Melissa Officinalis (Lemon Balm) Leaf Extract, Nigella Sativa (Black Cumin) Seed Oil, Silica, Tocopheryl Acetate, Triethanolamine, Water